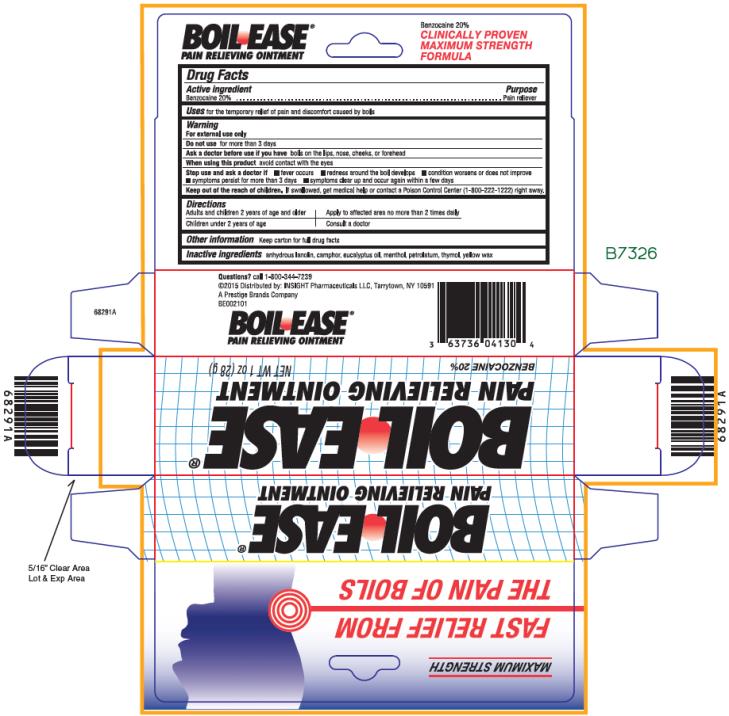 DRUG LABEL: Boil Ease
NDC: 63736-040 | Form: OINTMENT
Manufacturer: Insight Pharmaceuticals LLC
Category: otc | Type: HUMAN OTC DRUG LABEL
Date: 20241025

ACTIVE INGREDIENTS: BENZOCAINE 20 g/100 g
INACTIVE INGREDIENTS: LANOLIN; CAMPHOR (SYNTHETIC); EUCALYPTUS OIL; MENTHOL; PETROLATUM; THYMOL; YELLOW WAX

Boil Ease Ointment - 63736-040

BOIL EASE®
PAIN RELIEVING OINTMENT

Drug Facts

Active ingredient

Benzocaine 20%

Purpose

Pain Reliever

Use

for the temporary relief of pain and discomfort caused by boils

Warning

For external use only

Do not use

for more than 3 days

Ask a doctor before use if you have

boils on the lips, nose, cheeks, or forehead

When using this product

avoid contact with the eyes

Stop use and ask a doctor if

- fever occurs
- redness around the boil develops
- condition worsens or does not improve
- symptoms persist for more than 3 days
- symptoms clear up and occur again within a few days

Keep out of the reach of children.

If swallowed, get medical help or contact a Poison Control Center (1-800-222-1222) right away.

Directions

Adults and children 2 years of age and older | Apply to affected area no more than 2 times daily
Children under 2 years of age | Consult a doctor

Other information

Keep carton for full drug facts

Inactive ingredients

anhydrous lanolin, camphor, eucalyptus oil, menthol, petrolatum, thymol, yellow wax

Questions?

call 1-800-344-7239

PRINCIPAL DISPLAY PANEL

28 g Tube Carton
BOIL EASE®
PAIN RELIEVING OINTMENT
BENZOCAINE 20%
NET WT 1 oz (28 g)